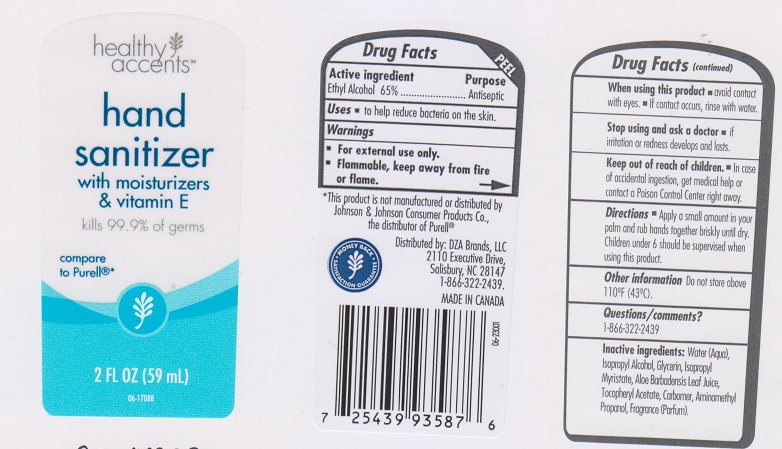 DRUG LABEL: Hand Sanitizer
NDC: 55316-253 | Form: GEL
Manufacturer: DZA Brands LLC
Category: otc | Type: HUMAN OTC DRUG LABEL
Date: 20170428

ACTIVE INGREDIENTS: ALCOHOL 650 mg/1 mL
INACTIVE INGREDIENTS: WATER; ISOPROPYL ALCOHOL; GLYCERIN; ISOPROPYL MYRISTATE; ALOE VERA LEAF; .ALPHA.-TOCOPHEROL ACETATE, DL-; AMINOMETHYLPROPANOL

Drug Facts

Active ingredient

Ethyl Alcohol 65%

Purpose

Antiseptic

Uses

- to help reduce bacteria on the skin

Warnings

- For external use only.
- Flammable, keep away from fire or flame

When using this product

- avoid contact with eyes.
- if contact occurs, rinse with water.

Stop using and ask a doctor

- if irritation or redness develops and lasts.

Keep out of reach of children.

- In case of accidental ingestion, get medical help or contact a Poison Control Center right away.

Directions

- apply a small amount in your palm and rub hands together briskly until dry. Children under 6 should be supervised when using this product.

Other information

do not store above 110°F (43°C)

Questions/comments?

1-866-322-2439

Inactive ingredients

Water (Aqua), Isopropyl Alcohol, Glycerin, Isopropyl Myristate, Aloe Barbadensis Leaf Juice, Tocopheryl Actate, Carbomer, Aminomethyl Propanol, Fragrance (Parfum).